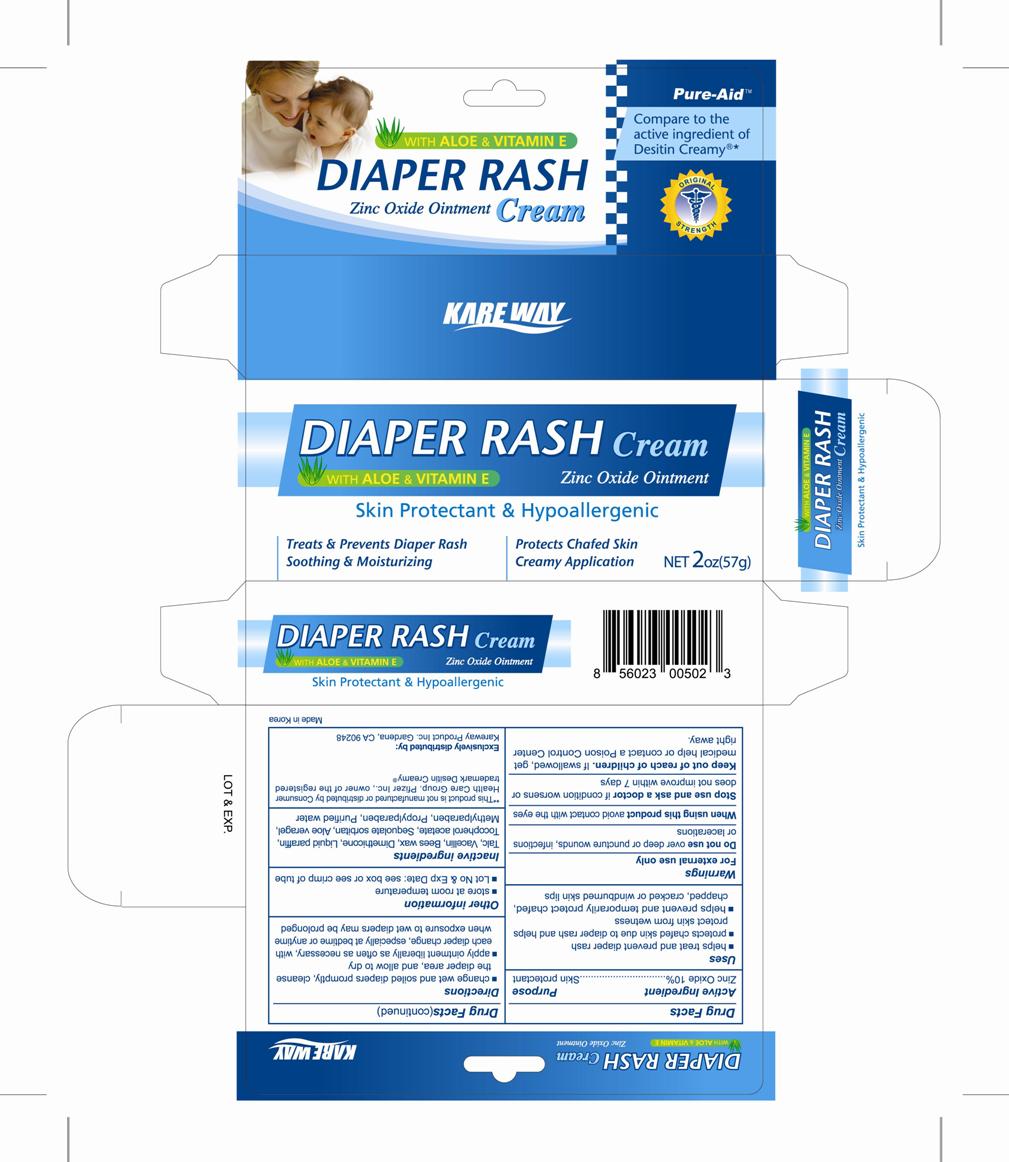 DRUG LABEL: Diaper Rash
NDC: 67510-0502 | Form: CREAM
Manufacturer: Kareway Product, Inc.
Category: otc | Type: HUMAN OTC DRUG LABEL
Date: 20201230

ACTIVE INGREDIENTS: ZINC OXIDE 0.1 g/1 g
INACTIVE INGREDIENTS: TALC; AMPICILLIN TRIHYDRATE; PEG-12 DIMETHICONE; MINERAL OIL; TOCOPHEROL; SORBITAN SESQUIOLEATE; ALOE VERA LEAF; METHYLPARABEN; PROPYLPARABEN; WATER

Pure-Aid Diaper Rash Cream

Active ingredient

Zinc Oxide 10%

Purpose

Skin Protectant

Uses

- helps treat and prevent diaper rash
- protects chafed skin due to diaper rash and helps protect skin from wetness
- helps prevent and temporarily protect chafed, chapped, cracked or windburned skin lips

Warnings

For external use only

Do not use

over deep or puncture wounds, infections or lacerations

When using this product

avoid contact with the eyes

Stop use and ask a doctor

if condition worsens or does not improve within 7 days.

Keep out of reach of children.

If swallowed, get medical help or contact a Poison Control Center right away.

Directions

- change wet and soiled diapers promptly, cleanse the diaper area, and allow to dry
- apply ointment liberally as often as necessary, with each diaper change, especially at bedtime or anytime when exposure to wet diapers may be prolonged

Other information

- store at room temperature
- Lot No and Exp Date: see box or see crimp of tube

Inactive ingredients

Talc, Vacillin, Bees wax, Demethicone, Liquid paraffin, Tocopherol acetate, Sesquioleate sorbitan, Aloe vera gel, Methylparaben, Propylparaben, Purified water

Package label

Diaper Rash Cream